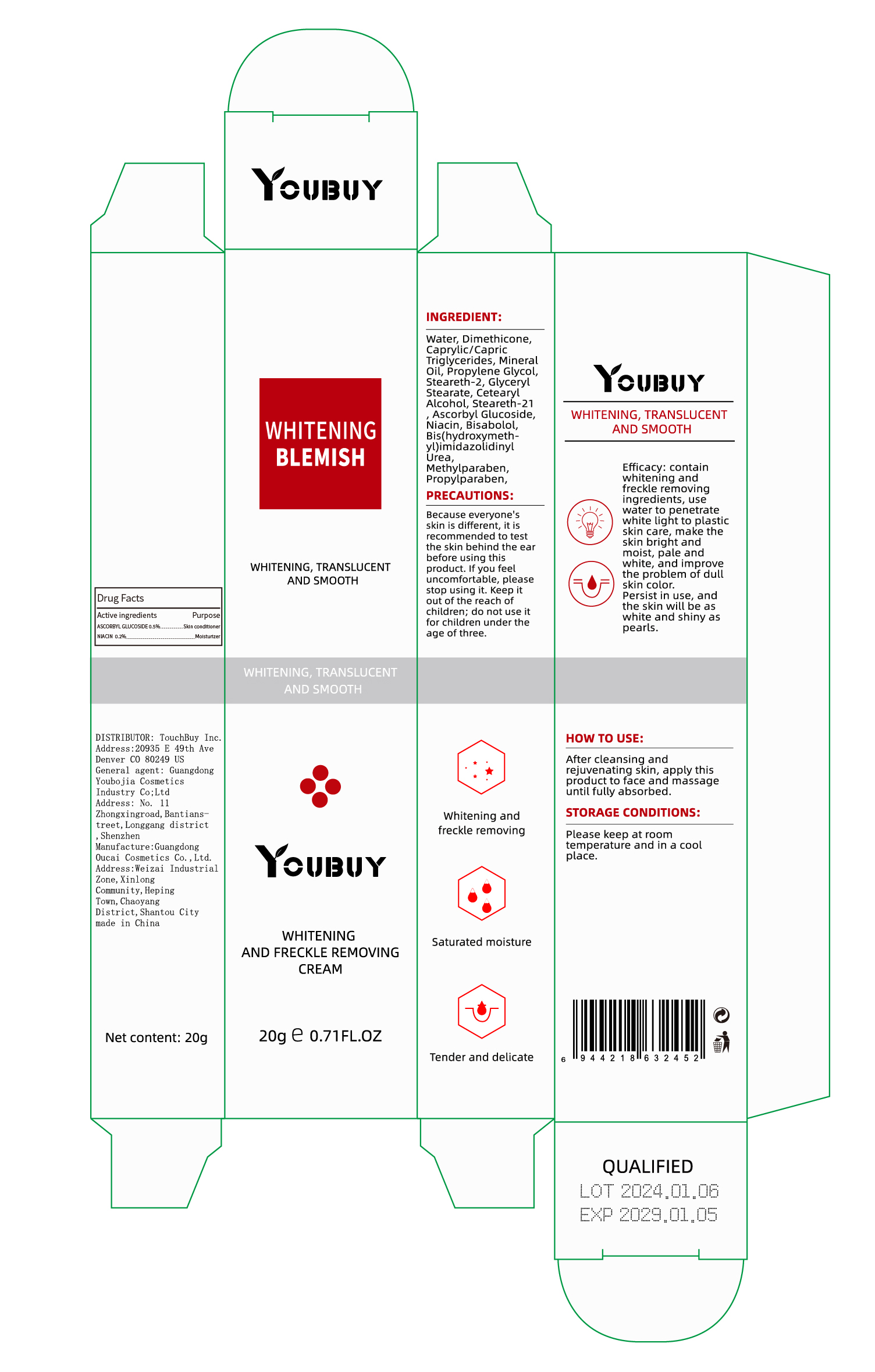 DRUG LABEL: YOUBUY Whitening and Freckle Removing Cream
NDC: 84712-013 | Form: CREAM
Manufacturer: Guangdong Youbaijia Cosmetic Industry Co., Ltd
Category: otc | Type: HUMAN OTC DRUG LABEL
Date: 20240914

ACTIVE INGREDIENTS: ASCORBYL GLUCOSIDE 0.1 g/20 g; NIACIN 0.04 g/20 g
INACTIVE INGREDIENTS: MINERAL OIL 0.07 g/20 g; STEARETH-2 0.05 g/20 g

ACTIVE INGREDIENT

ASCORBYL GLUCOSIDE 0.5%
NIACIN 0.2%

INACTIVE INGREDIENT

Water
DIMETHICONE
CAPRYLIC/CAPRIC TRIGLYCERIDE
MINERAL OIL
PROPYLENE GLYCOL
STEARETH-2
GLYCERYL STEARATE
CETEARYL ALCOHOL
STEARETH-21
BISABOLOL
Bis(hydroxymeth-yl)imidazolidinyl Urea
METHYLPARABEN
PROPYLPARABEN

Do not use on damaged skin.

Keep away from children. Do not swallow.

PURPOSE

WHITENING AND FRECKLE REMOVING

QUESTIONS

Contact name: Jessie Peng
Company phone number: +1 818 579 7288
Company e-mail: jessie@registeragentllc.com

STOP USE

lf skin becomes red or irritated, discontinue use immediately and wash with water.

WHEN USING

keep out of eyes. Rinse with water to remove.

STORAGE AND HANDLING

Keep away from light and in adry place.

WARNINGS

For external use only.

INDICATIONS AND USAGE

contain whitening and freckle removing ingredients,use water to penetrate white light to plastic skin care, make the skin bright and moist, pale and white,and improve the problem of dull skin color.Persist in use, and the skin will be as white and shiny aspearls.

DOSAGE AND ADMINISTRATION

After cleansing and rejuvenating skin, apply this product to face and massage until fully absorbed.